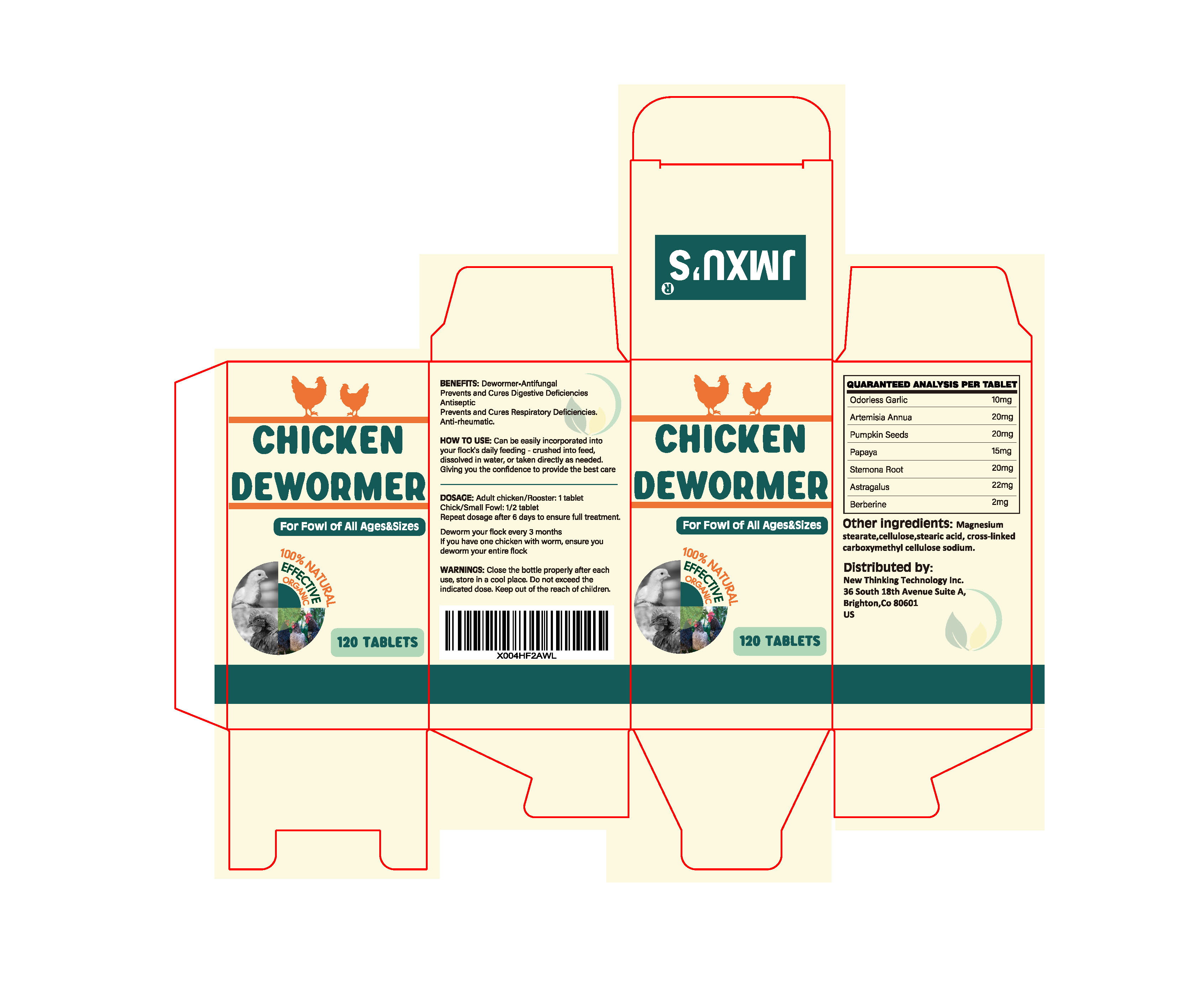 DRUG LABEL: Chicken dewormer
NDC: 86216-001 | Form: TABLET
Manufacturer: Pet Professional inc.
Category: animal | Type: OTC ANIMAL DRUG LABEL
Date: 20250116

ACTIVE INGREDIENTS: GARLIC 10 mg/1 1; ARTEMISIA ANNUA WHOLE 20 mg/1 1; PUMPKIN SEED 20 mg/1 1; PAPAYA 15 mg/1 1

chicken dewormer

WARNINGS AND PRECAUTIONS SECTION

WARNINGS: Close the bottle properly after each use, store in a cool place. Do not exceed the indicated dose. Keep out of the reach of children.

Content of Labling